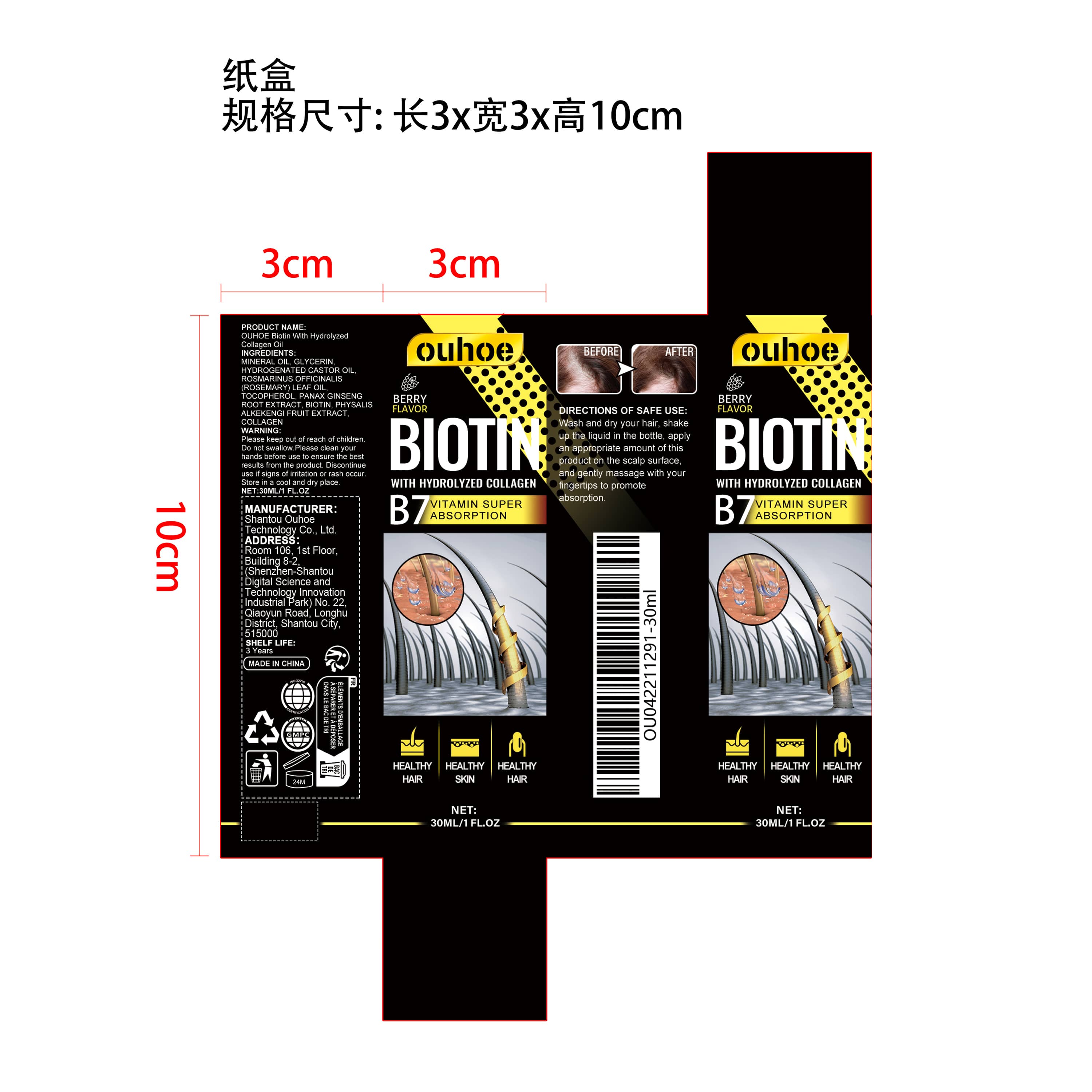 DRUG LABEL: OUHOE Biotin With Hydrolyzed Collagen
NDC: 85163-011 | Form: LIQUID
Manufacturer: Shantou Ouhoe Technology Co., Ltd.
Category: otc | Type: HUMAN OTC DRUG LABEL
Date: 20251127

ACTIVE INGREDIENTS: PHYSALIS ALKEKENGI FRUIT 0.006 mg/30 mg; ROSMARINUS OFFICINALIS (ROSEMARY) LEAF OIL 0.06 mg/30 mg; HYDROGENATED CASTOR OIL 0.3 mg/30 mg; PANAX GINSENG ROOT 0.03 mg/30 mg; MINERAL OIL 27.162 mg/30 mg
INACTIVE INGREDIENTS: BIOTIN 0.006 mg/30 mg; TOCOPHEROL 0.03 mg/30 mg; 1-BUTYLGLYCERIN 2.4 mg/30 mg; COLLAGEN ALPHA-1(I) CHAIN BOVINE 0.006 mg/30 mg

ACTIVE INGREDIENT

MINERAL OIL、HYDROGENATED CASTOR OIL、ROSMARINUS OFFICINALIS (ROSEMARY) LEAF OIL、PANAX GINSENG ROOT EXTRACT、PHYSALIS ALKEKENGI FRUIT EXTRACT

PURPOSE

1. It can strengthen hair quality. effectively prevent hair loss, nourish hair roots and promote hair growth.

2. Repair damaged hair follicles, improve dry and damaged hair, and make your hair full of life.

3. Helps balance oil, prevent the formation of dandruff, and protect scalp health.

4. Mild formula, will not burden the scalp and hair, and promotes the health of your hair

WHEN USING

Wash and dry your hair, shake up the liquid in the bottle, apply an appropriate amount of this product on the scalp surface, and gently massage with your fingertips to promote absorption.

WARNINGS

Please keep out of reach of children. Do not swallow.Please clean your hands before use to ensure the best results from the product. Discontinue use if signs of irritation or rash occur. Store in a cool and dry place.

DO NOT USE

Discontinue use if signs of irritation or rash occur.

STOP USE

Discontinue use if signs of irritation or rash occur.

KEEP OUT OF REACH OF CHILDREN

Please keep out of reach of children. Do not swallow.

STORAGE AND HANDLING

Store in a cool and dry place.

INACTIVE INGREDIENT

GLYCERIN、TOCOPHEROL、BIOTIN、COLLAGEN

INDICATIONS AND USAGE

Wash and dry your hair, shake up the liquid in the bottle, apply an appropriate amount of this product on the scalp surface, and gently massage with your fingertips to promote absorption.

DOSAGE AND ADMINISTRATION

Wash and dry your hair, shake up the liquid in the bottle, apply an appropriate amount of this product on the scalp surface, and gently massage with your fingertips to promote absorption.